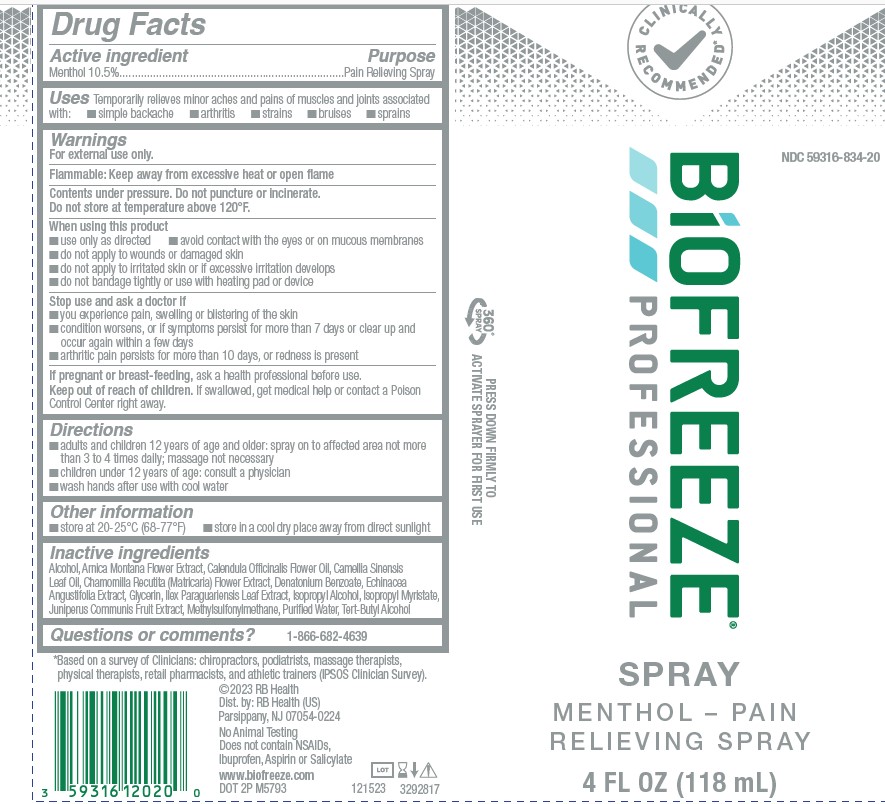 DRUG LABEL: Biofreeze Professional
NDC: 59316-834 | Form: AEROSOL, SPRAY
Manufacturer: RB Health (US) LLC
Category: otc | Type: HUMAN OTC DRUG LABEL
Date: 20250205

ACTIVE INGREDIENTS: MENTHOL, UNSPECIFIED FORM 105 mg/1 mL
INACTIVE INGREDIENTS: ALCOHOL; ARNICA MONTANA FLOWER; CALENDULA OFFICINALIS FLOWER; TEA LEAF OIL; CHAMOMILE; DIMETHYL SULFONE; ECHINACEA ANGUSTIFOLIA WHOLE; ILEX PARAGUARIENSIS LEAF; ISOPROPYL MYRISTATE; JUNIPER BERRY; WATER; DENATONIUM BENZOATE; GLYCERIN; TERT-BUTYL ALCOHOL; ISOPROPYL ALCOHOL

Biofreeze®Professional Spray

Drug Facts

Active ingredient

Menthol 10.5%

Purpose

Pain Relieving Spray

Uses

Temporarily relieves minor aches and pains of muscles and joints associated with:

- simple backache
- arthritis
- strains
- bruises
- sprains

Warnings

For external use only.

Flammable:Keep away from excessive heat or open flame

Contents under pressure. Do not puncture or incinerate.

Do not store at temperature above 120°F.

When using this product

- use only as directed
- avoid contact with the eyes or on mucous membranes
- do not apply to wounds or damaged skin
- do not apply to irritated skin or if excessive irritation develops
- do not bandage tightly or use with heating pad or device

Stop use and ask a doctor if

- you experience pain, swelling or blistering of the skin
- condition worsens, or if symptoms persist for more than 7 days or clear up and occur again within a few days
- arthritic pain persists for more than 10 days, or redness is present

PREGNANCY OR BREAST FEEDING

If pregnant or breast-feeding,ask a health professional before use.

Keep out of reach of children.If swallowed, get medical help or contact a Poison Control Center right away.

Directions

- adults and children 12 years of age and older: spray on to affected area not more than 3 to 4 times daily; massage not necessary
- children under 12 years of age: consult a physician
- wash hands after use with cool water

Other information

- store at 20-25°C (68-77°F)
- store in a cool dry place away from direct sunlight

Inactive ingredients

Alcohol, Arnica Montana Flower Extract, Calendula Officinalis Flower Oil, Camellia Sinensis
Leaf Oil, Chamomilla Recutita (Matricaria) Flower Extract, Denatonium Benzoate, Echinacea
Angustifolia Extract, Glycerin, Ilex Paraguariensis Leaf Extract, Isopropyl Alcohol, Isopropyl Myristate,
Juniperus Communis Fruit Extract, Methylsulfonylmethane, PurifiedWater, Tert-Butyl Alcohol

Questions or comments?

1-800-246-3733

Dist. by: RB Health (US), Parsippany, NJ 07054-0224

PRINCIPAL DISPLAY PANEL - 118 mL Bottle Label

CLINICALLY
RECOMMENDED*

NDC 59316-834-20

BiOFREEZE®
PROFESSIONAL

SPRAY
MENTHOL-PAIN
RELIEVING SPRAY

4 FL OZ (118 mL)

360°
SPRAY

PRESS DOWN FIRMLY TO
ACTIVATE SPRAYER FOR FIRST USE